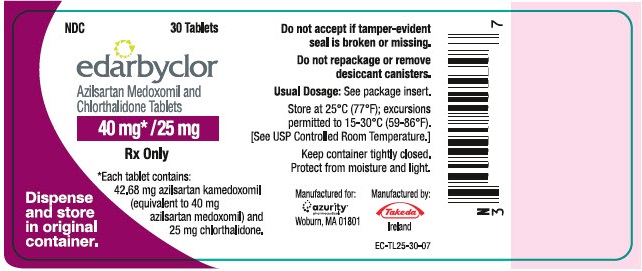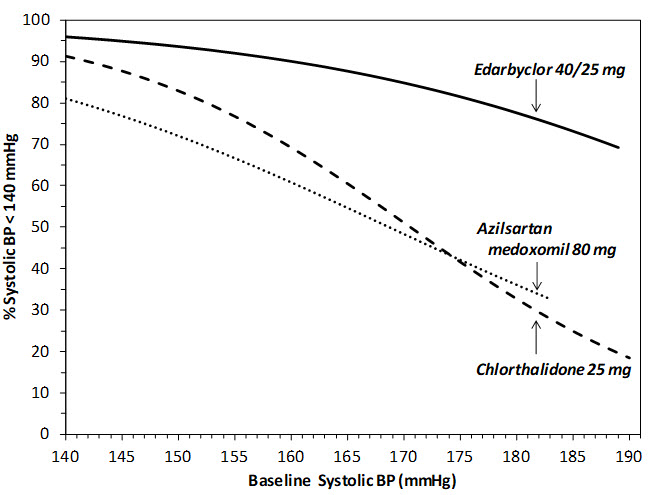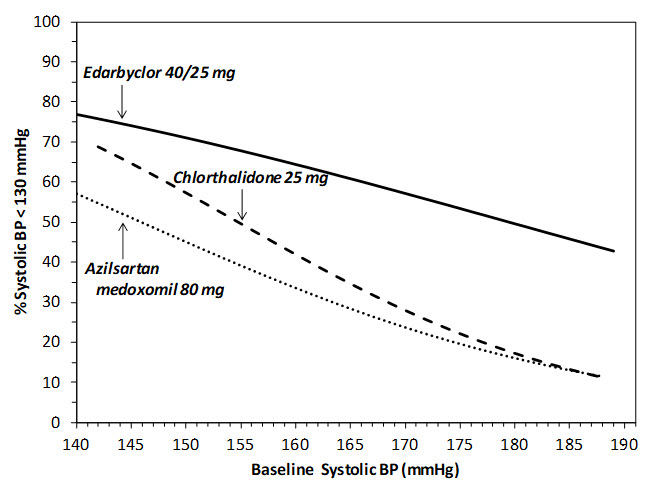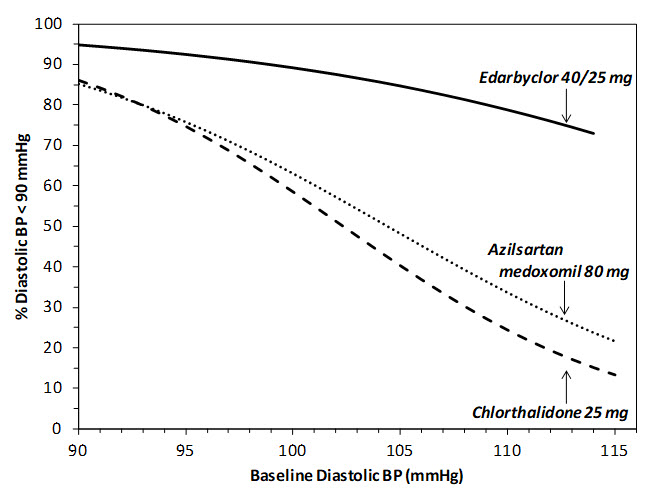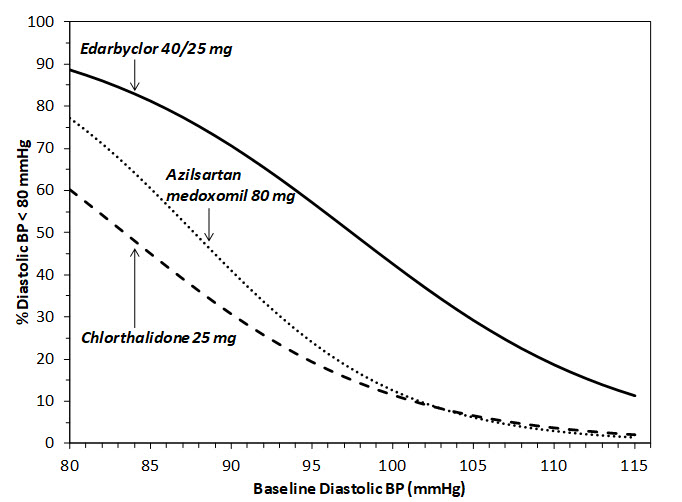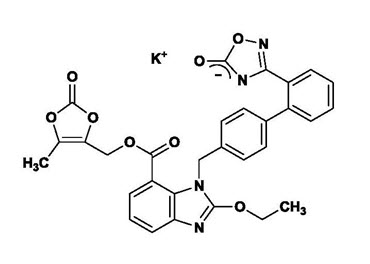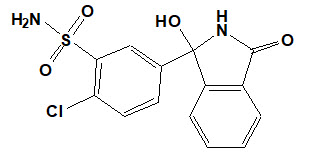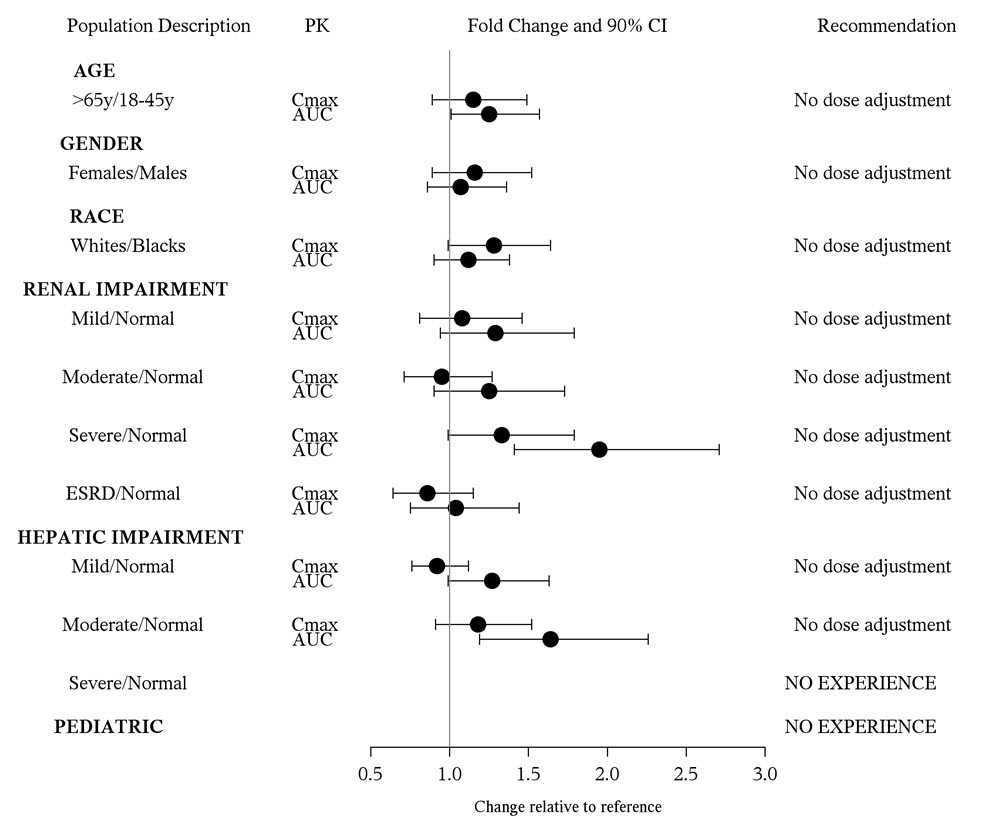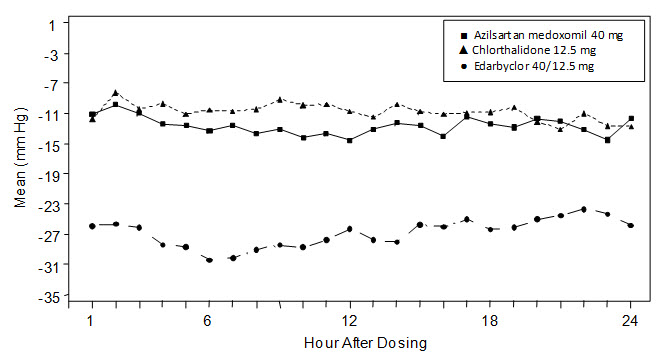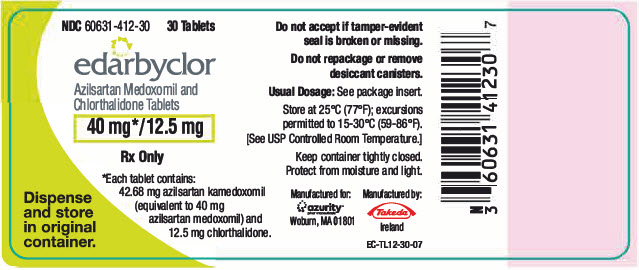 DRUG LABEL: Edarbyclor
NDC: 75929-230 | Form: TABLET
Manufacturer: Pharma Packaging Solutions, LLC dba Tjoapack LLC
Category: prescription | Type: HUMAN PRESCRIPTION DRUG LABEL
Date: 20250723

ACTIVE INGREDIENTS: AZILSARTAN KAMEDOXOMIL 40 mg/1 1; CHLORTHALIDONE 25 mg/1 1
INACTIVE INGREDIENTS: MANNITOL; MICROCRYSTALLINE CELLULOSE; TALC; TITANIUM DIOXIDE; FERRIC OXIDE RED; POLYETHYLENE GLYCOL 8000; BUTYL ALCOHOL; CROSPOVIDONE (120 .MU.M); WATER; FUMARIC ACID; SODIUM HYDROXIDE; HYDROXYPROPYL CELLULOSE (1600000 WAMW); MAGNESIUM STEARATE; HYPROMELLOSE, UNSPECIFIED; SHELLAC; FERROSOFERRIC OXIDE; ALCOHOL

HIGHLIGHTS OF PRESCRIBING INFORMATION

EDARBYCLOR (azilsartan medoxomil and chlorthalidone) tablets, for oral use
(Packaged by Pharma Packaging Solutions, LLC dba Tjoapack LLC)
These highlights do not include all the information needed to use EDARBYCLOR safely and effectively. See full prescribing information for EDARBYCLOR.
Initial U.S. Approval: 2011

WARNING: FETAL TOXICITY

See full prescribing information for complete boxed warning.

- When pregnancy is detected, discontinue EDARBYCLOR as soon as possible (5.1, 8.1)
- Drugs that act directly on the renin-angiotensin system can cause injury and death to the developing fetus (5.1, 8.1)

1 INDICATIONS AND USAGE

Edarbyclor is a combination of azilsartan medoxomil, an angiotensin II receptor blocker (ARB) and chlorthalidone, a thiazide-like diuretic combination product indicated for the treatment of hypertension, to lower blood pressure:

- In patients not adequately controlled with monotherapy (1)
- As initial therapy in patients likely to need multiple drugs to help achieve blood pressure goals (1)

Lowering blood pressure reduces the risk of fatal and nonfatal cardiovascular events, primarily strokes and myocardial infarctions (1)

2 DOSAGE AND ADMINISTRATION

- Starting dose is 40/12.5 mg once daily (2.1)
- Edarbyclor may be used to provide additional blood pressure lowering for patients not adequately controlled on azilsartan medoxomil 80 mg or chlorthalidone 25 mg (2.1)
- Dose may be increased to 40/25 mg after 2 to 4 weeks as needed to achieve blood pressure goals (2.1)
- Maximal dose is 40/25 mg (2.1)
- May be administered with other antihypertensive agents (2.1)
- Edarbyclor may be administered with or without food (2.1)
- Replace volume in volume-depleted patients prior to use (2.2)

3 DOSAGE FORMS AND STRENGTHS

Tablets (azilsartan/chlorthalidone): 40/12.5 mg and 40/25 mg (3)

4 CONTRAINDICATIONS

- Anuria (4)
- Do not coadminister aliskiren-containing products with Edarbyclor in patients with diabetes (4)

5 WARNINGS AND PRECAUTIONS

- In patients with an activated renin-angiotensin-aldosterone system (RAAS), such as volume- and/or salt-depleted patients, Edarbyclor can cause excessive hypotension. Correct volume or salt depletion prior to administration of Edarbyclor (5.2)
- In patients with renal artery stenosis, Edarbyclor may cause renal failure (5.3)
- Monitor renal function in patients with renal impairment. Consider discontinuing Edarbyclor with progressive renal impairment (5.3)
- Monitor serum electrolytes periodically (5.4)

6 ADVERSE REACTIONS

Most common adverse reactions (incidence ≥2%) are dizziness and fatigue (6.1)

To report SUSPECTED ADVERSE REACTIONS, contact Azurity Pharmaceuticals, Inc. at 1-800-461-7449 or FDA at 1-800-FDA-1088 or www.fda.gov/medwatch.

7 DRUG INTERACTIONS

- Renal clearance of lithium is reduced by diuretics, such as chlorthalidone increasing the risk of lithium toxicity (7)
- NSAIDS increase risk of renal dysfunction and interfere with antihypertensive effect (7)
- Dual inhibition of the renin-angiotensin system: Increased risk of renal impairment, hypotension, and hyperkalemia (7)
- Lithium: Increases in serum lithium concentrations and lithium toxicity (7)

8 USE IN SPECIFIC POPULATIONS

Lactation: Breastfeeding is not recommended. (8.2)

FULL PRESCRIBING INFORMATION

WARNING: FETAL TOXICITY

- When pregnancy is detected, discontinue Edarbyclor as soon as possible [see Warnings and Precautions (5.1)and Use in Specific Populations (8.1)].
- Drugs that act directly on the renin-angiotensin system can cause injury and death to the developing fetus [see Warnings and Precautions (5.1)and Use in Specific Populations (8.1)].

1 INDICATIONS AND USAGE

Edarbyclor is indicated for the treatment of hypertension, to lower blood pressure.

Edarbyclor may be used in patients whose blood pressure is not adequately controlled on monotherapy.

Edarbyclor may be used as initial therapy if a patient is likely to need multiple drugs to achieve blood pressure goals.

Lowering blood pressure reduces the risk of fatal and nonfatal cardiovascular events, primarily strokes and myocardial infarctions. These benefits have been seen in controlled trials of antihypertensive drugs from a wide variety of pharmacologic classes including thiazide-like diuretics such as chlorthalidone and ARBs such as azilsartan medoxomil. There are no controlled trials demonstrating risk reduction with Edarbyclor.

Control of high blood pressure should be part of comprehensive cardiovascular risk management, including, as appropriate, lipid control, diabetes management, antithrombotic therapy, smoking cessation, exercise, and limited sodium intake. Many patients will require more than one drug to achieve blood pressure goals. For specific advice on goals and management of high blood pressure, see published guidelines, such as those of the National High Blood Pressure Education Program's Joint National Committee on Prevention, Detection, Evaluation, and Treatment of High Blood Pressure (JNC).

Numerous antihypertensive drugs, from a variety of pharmacologic classes and with different mechanisms of action, have been shown in randomized controlled trials to reduce cardiovascular morbidity and mortality, and it can be concluded that it is blood pressure reduction, and not some other pharmacologic property of the drugs, that is largely responsible for those benefits. The largest and most consistent cardiovascular outcome benefit has been a reduction in the risk of stroke, but reductions in myocardial infarction and cardiovascular mortality also have been seen regularly.

Elevated systolic or diastolic pressure causes increased cardiovascular risk, and the absolute risk increase per mmHg is greater at higher blood pressures, so that even modest reductions of severe hypertension can provide substantial benefit. Relative risk reduction from blood pressure reduction is similar across populations with varying absolute risk, so the absolute benefit is greater in patients who are at higher risk independent of their hypertension (for example, patients with diabetes or hyperlipidemia), and such patients would be expected to benefit from more aggressive treatment to a lower blood pressure goal.

Some antihypertensive drugs have smaller blood pressure effects (as monotherapy) in black patients; however, the blood pressure effect of Edarbyclor in blacks is similar to that in non-blacks. Many antihypertensive drugs have additional approved indications and effects (e.g., on angina, heart failure, or diabetic kidney disease). These considerations may guide selection of therapy.

The choice of Edarbyclor as initial therapy for hypertension should be based on an assessment of potential benefits and risks including whether the patient is likely to tolerate the starting dose of Edarbyclor.

Patients with moderate-to-severe hypertension are at a relatively high risk of cardiovascular events (e.g., stroke, heart attack, and heart failure), kidney failure, and vision problems, so prompt treatment is clinically relevant. Consider the patient's baseline blood pressure, target goal and the incremental likelihood of achieving the goal with a combination product, such as Edarbyclor, versus a monotherapy product when deciding upon initial therapy. Individual blood pressure goals may vary based on the patient's risk.

Data from an 8-week, active-controlled, factorial trial provide estimates of the probability of reaching a target blood pressure with Edarbyclor compared with azilsartan medoxomil or chlorthalidone monotherapy [see Clinical Studies (14)] .

Figures 1.a-1.d provide estimates of the likelihood of achieving target clinic systolic and diastolic blood pressure control with Edarbyclor 40/25 mg tablets after 8 weeks, based on baseline systolic or diastolic blood pressure. The curve for each treatment group was estimated by logistic regression modeling and is more variable at the tails.

Figure 1.a Probability of Achieving Systolic Blood Pressure <140 mmHg at Week 8

Figure 1.b Probability of Achieving Systolic Blood Pressure <130 mmHg at Week 8

Figure 1.c Probability of Achieving Diastolic Blood Pressure <90 mmHg at Week 8

Figure 1.d Probability of Achieving Diastolic Blood Pressure <80 mmHg at Week 8

For example, a patient with a baseline blood pressure of 170/105 mm Hg has approximately a 48% likelihood of achieving a goal of <140 mm Hg (systolic) and 48% likelihood of achieving <90 mm Hg (diastolic) on azilsartan medoxomil 80 mg. The likelihood of achieving these same goals on chlorthalidone 25 mg is approximately 51% (systolic) and 40% (diastolic). These likelihoods rise to 85% (systolic) and 85% (diastolic) with Edarbyclor 40/25 mg.

2 DOSAGE AND ADMINISTRATION

2.1 Dosing Information

The recommended starting dose of Edarbyclor is 40/12.5 mg taken orally once daily. Most of the antihypertensive effect is apparent within 1 to 2 weeks. The dosage may be increased to 40/25 mg after 2 to 4 weeks as needed to achieve blood pressure goals. Edarbyclor doses above 40/25 mg are probably not useful.

Patients titrated to the individual components (azilsartan medoxomil and chlorthalidone) may instead receive the corresponding dose of Edarbyclor.

Edarbyclor may be administered with other antihypertensive agents as needed.

2.2 Prior to Dosing

Correct any volume depletion prior to administration of Edarbyclor, particularly in patients with impaired renal function or those treated with high doses of diuretics [see Warnings and Precautions (5.2)].

Patients who experience dose-limiting adverse reactions on chlorthalidone may be switched to Edarbyclor, initially with a lower dose of chlorthalidone [see Warnings and Precautions (5.4)].

2.3 Handling Instructions

Do not repackage Edarbyclor. Dispense and store Edarbyclor in its original container to protect Edarbyclor from light and moisture.

3 DOSAGE FORMS AND STRENGTHS

Edarbyclor is supplied in the following dosage strengths:

- 40/12.5 mg: pale red, round, biconvex, film-coated tablets, approximately 9.7 mm in diameter, with "A/C" and "40/12.5" imprinted on one side. Each tablet contains 40 mg of azilsartan medoxomil and 12.5 mg of chlorthalidone.
- 40/25 mg: light red, round, biconvex, film-coated tablets, approximately 9.7 mm in diameter, with "A/C" and "40/25" imprinted on one side. Each tablet contains 40 mg of azilsartan medoxomil and 25 mg of chlorthalidone.

4 CONTRAINDICATIONS

- Edarbyclor is contraindicated in patients with anuria [see Warnings and Precautions (5.3)].
- Do not coadminister aliskiren-containing products with Edarbyclor in patients with diabetes [see Drug Interactions (7)] .

5 WARNINGS AND PRECAUTIONS

5.1 Fetal Toxicity

Azilsartan medoxomil

Edarbyclor can cause fetal harm when administered to a pregnant woman. Use of drugs that act on the renin-angiotensin system during the second and third trimesters of pregnancy reduces fetal renal function and increases fetal and neonatal morbidity and death. Resulting oligohydramnios can be associated with fetal lung hypoplasia and skeletal deformations. Potential neonatal adverse effects include skull hypoplasia, anuria, hypotension, renal failure, and death. When pregnancy is detected, discontinue Edarbyclor as soon as possible [see Use in Specific Populations (8.1)].

Chlorthalidone

Thiazides cross the placental barrier and appear in cord blood. Adverse reactions include fetal or neonatal jaundice and thrombocytopenia.

5.2 Hypotension in Volume- or Salt-Depleted Patients

In patients with an activated renin-angiotensin system, such as volume- or salt-depleted patients (e.g., those being treated with high doses of diuretics), symptomatic hypotension may occur after initiation of treatment with Edarbyclor. Such patients are probably not good candidates to start therapy with more than one drug; therefore, correct volume prior to administration of Edarbyclor. If hypotension does occur, the patient should be placed in the supine position and, if necessary, given an intravenous infusion of normal saline .A transient hypotensive response is not a contraindication to further treatment, which usually can be continued without difficulty once the blood pressure has stabilized.

5.3 Impaired Renal Function

Edarbyclor

Monitor for worsening renal function in patients with renal impairment. Consider withholding or discontinuing Edarbyclor if progressive renal impairment becomes evident .

Azilsartan medoxomil

As a consequence of inhibiting the renin-angiotensin system, changes in renal function may be anticipated in susceptible individuals treated with Edarbyclor. In patients whose renal function may depend on the activity of the renin-angiotensin system (e.g., patients with severe congestive heart failure, renal artery stenosis, or volume depletion), treatment with angiotensin-converting enzyme inhibitors and angiotensin receptor blockers has been associated with oliguria or progressive azotemia and rarely with acute renal failure and death. Similar results may be anticipated in patients treated with Edarbyclor [see Drug Interactions (7), Use in Specific Populations (8.6)and Clinical Pharmacology (12.3)].

In studies of ACE inhibitors in patients with unilateral or bilateral renal artery stenosis, increases in serum creatinine or blood urea nitrogen have been reported. There has been no long-term use of azilsartan medoxomil in patients with unilateral or bilateral renal artery stenosis, but similar results are expected.

Chlorthalidone

In patients with renal disease, chlorthalidone may precipitate azotemia. If progressive renal impairment becomes evident, as indicated by increased blood urea nitrogen, consider withholding or discontinuing diuretic therapy.

5.4 Serum Electrolyte Imbalances

Thiazide diuretics can cause hyponatremia and hypokalemia. Drugs that inhibit the renin angiotensin system can cause hyperkalemia. Hypokalemia is a dose-dependent adverse reaction that may develop with chlorthalidone. Co-administration of digitalis may exacerbate the adverse effects of hypokalemia. Monitor serum electrolytes periodically.

Edarbyclor attenuates chlorthalidone-associated hypokalemia. In patients with normal potassium levels at baseline, 1.7% of Edarbyclor-treated patients, 0.9% of azilsartan medoxomil-treated patients, and 13.4% of chlorthalidone-treated patients shifted to low potassium values (less than 3.4 mmol/L).

5.5 Hyperuricemia

Chlorthalidone

Hyperuricemia may occur or frank gout may be precipitated in certain patients receiving chlorthalidone or other thiazide diuretics.

6 ADVERSE REACTIONS

The following potential adverse reactions with Edarbyclor, azilsartan medoxomil, or chlorthalidone and similar agents are included in more detail in the Warnings and Precautions section of the label:

- Fetal toxicity [see Warnings and Precautions (5.1)]
- Hypotension in Volume- or Salt-Depleted Patients [see Warnings and Precautions (5.2)]
- Impaired Renal Function [see Warnings and Precautions (5.3)]
- Hypokalemia [see Warnings and Precautions (5.4)]
- Hyperuricemia [see Warnings and Precautions (5.5)]

6.1 Clinical Trials Experience

Because clinical trials are conducted under widely varying conditions, adverse reaction rates observed in the clinical trials of a drug cannot be directly compared to rates in the clinical trials of another drug and may not reflect the rates observed in practice.

Edarbyclor has been evaluated for safety in more than 3900 patients with hypertension; more than 700 patients were treated for at least 6 months and more than 280 for at least 1 year. Adverse reactions have generally been mild and transient in nature.

Common adverse reactions that occurred in the 8-week factorial design trial in at least 2% of Edarbyclor-treated patients and greater than azilsartan medoxomil or chlorthalidone are presented in Table 1.

Table 1. Adverse Reactions Occurring at an Incidence of ≥2% of Edarbyclor-treated Patients and > Azilsartan medoxomil or Chlorthalidone
Preferred Term | Azilsartan medoxomil 20, 40, 80 mg (N=470) | Chlorthalidone 12.5, 25 mg (N=316) | Edarbyclor 40 / 12.5, 40 / 25 mg (N=302)
Dizziness | 1.7% | 1.9% | 8.9%
Fatigue | 0.6% | 1.3% | 2.0%

Hypotension and syncope were reported in 1.7% and 0.3%, respectively, of patients treated with Edarbyclor.

Study discontinuation because of adverse reactions occurred in 8.3% of patients treated with the recommended doses of Edarbyclor compared with 3.2% of patients treated with azilsartan medoxomil and 3.2% of patients treated with chlorthalidone. The most common reasons for discontinuation of therapy with Edarbyclor were serum creatinine increased (3.6%) and dizziness (2.3%).

The adverse reaction profile obtained from 52 weeks of open-label combination therapy with azilsartan medoxomil plus chlorthalidone or Edarbyclor was similar to that observed during the double-blind, active controlled trials.

In 3 double-blind, active controlled, titration studies, in which Edarbyclor was titrated to higher doses in a step-wise manner, adverse reactions and discontinuations for adverse events were less frequent than in the fixed-dose factorial trial.

Azilsartan medoxomil

A total of 4814 patients were evaluated for safety when treated with azilsartan medoxomil at doses of 20, 40 or 80 mg in clinical trials. This includes 1704 patients treated for at least 6 months, of these, 588 were treated for at least 1 year. Generally, adverse reactions were mild, not dose related and similar regardless of age, gender and race.

Adverse reactions with a plausible relationship to treatment that have been reported with an incidence of ≥0.3% and greater than placebo in more than 3300 patients treated with azilsartan medoxomil in controlled trials are listed below:

Gastrointestinal Disorders:diarrhea, nausea
General Disorders and Administration Site Conditions:asthenia, fatigue
Musculoskeletal and Connective Tissue Disorders:muscle spasm
Nervous System Disorders:dizziness, dizziness postural
Respiratory, Thoracic and Mediastinal Disorders:cough

Chlorthalidone

The following adverse reactions have been observed in clinical trials of chlorthalidone: rash, headache, dizziness, GI upset, and elevations of uric acid and cholesterol.

Clinical Laboratory Findings with Edarbyclor

In the factorial design trial, clinically relevant changes in standard laboratory parameters were uncommon with administration of the recommended doses of Edarbyclor.

Renal parameters:

The incidence of consecutive increases of creatinine ≥50% from baseline and >ULN was 2.0% in patients treated with the recommended doses of Edarbyclor compared with 0.4% and 0.3% with azilsartan medoxomil and chlorthalidone, respectively.

Mean increases in blood urea nitrogen (BUN) were observed with Edarbyclor (5.3 mg/dL) compared with azilsartan medoxomil (1.5 mg/dL) and with chlorthalidone (2.5 mg/dL).

6.2 Postmarketing Experience

The following adverse reactions have been identified during the postmarketing use of EDARBYCLOR. Because these reactions are reported voluntarily from a population of uncertain size, it is not always possible to reliably estimate their frequency or establish a causal relationship to drug exposure.

- Loss of consciousness
- Pruritus
- Angioedema

7 DRUG INTERACTIONS

7.1 Non-Steroidal Anti-Inflammatory Agents including Selective Cyclooxygenase-2 Inhibitors (COX-2 Inhibitors)

In patients who are elderly, volume-depleted (including those on diuretic therapy), or who have compromised renal function, co-administration of NSAIDs, including selective COX-2 inhibitors, with angiotensin II receptor antagonists, including azilsartan, may result in deterioration of renal function, including possible acute renal failure. These effects are usually reversible. Monitor renal function periodically in patients receiving Edarbyclor and NSAID therapy.

The antihypertensive effect of Edarbyclor may be attenuated by NSAIDs, including selective COX-2 inhibitors.

7.2 Dual Blockade of the Renin-Angiotensin System (RAS)

Dual blockade of the RAS with angiotensin receptor blockers, ACE inhibitors, or aliskiren is associated with increased risks of hypotension, hyperkalemia, and changes in renal function (including acute renal failure) compared to monotherapy. Most patients receiving the combination of two RAS inhibitors do not obtain any additional benefit compared to monotherapy. In general, avoid combined use of RAS inhibitors. Closely monitor blood pressure, renal function and electrolytes in patients on Edarbyclor and other agents that affect the RAS.

Do not coadminister aliskiren with Edarbyclor in patients with diabetes. Avoid use of aliskiren with Edarbyclor in patients with renal impairment (GFR <60 mL/min).

7.3 Lithium

Increases in serum lithium concentrations and lithium toxicity have been reported during concomitant administration of lithium with angiotensin II receptor agonists. Lithium renal clearance is reduced by diuretics, such as chlorthalidone. Monitor serum lithium levels during concomitant use.

8 USE IN SPECIFIC POPULATIONS

8.1 Pregnancy

Risk Summary

Edarbyclor can cause fetal harm when administered to a pregnant woman. Use of drugs that act on the renin-angiotensin system during the second and third trimesters of pregnancy reduces fetal renal function and increases fetal and neonatal morbidity and death (see Clinical Considerations). Most epidemiologic studies examining fetal abnormalities after exposure to antihypertensive use in the first trimester have not distinguished drugs affecting the renin-angiotensin system from other antihypertensive agents.

When pregnancy is detected, discontinue Edarbyclor as soon as possible.

The estimated background risk of major birth defects and miscarriage for the indicated population is unknown. All pregnancies have a background risk of birth defect, loss, or other adverse outcomes. In the U.S. general population, the estimated background risk of major birth defects and miscarriage in clinically recognized pregnancies is 2-4% and 15-20%, respectively.

Clinical Considerations

Disease-associated maternal and/or embryo/fetal risk

Hypertension in pregnancy increases the maternal risk for pre-eclampsia, gestational diabetes, premature delivery, and delivery complications (e.g., need for cesarean section, and post-partum hemorrhage). Hypertension increases the fetal risk for intrauterine growth restriction and intrauterine death. Pregnant women with hypertension should be carefully monitored and managed accordingly.

Fetal/Neonatal adverse reactions

Oligohydramnios in pregnant women who use drugs affecting the renin-angiotensin system in the second and third trimesters can result in the following: reduced fetal renal function leading to anuria and renal failure, fetal lung hypoplasia, skeletal deformations, including skull hypoplasia, hypotension and death.

Perform serial ultrasound examinations to assess the intra-amniotic environment. Fetal testing may be appropriate, based on the week of pregnancy. Patients and physicians should be aware, however, that oligohydramnios may not appear until after the fetus has sustained irreversible injury.

Closely observe infants with histories of in uteroexposure to Edarbyclor for hypotension, oliguria, and hyperkalemia. In neonates with a history of in uteroexposure to Edarbyclor, if oliguria or hypotension occurs, support blood pressure and renal perfusion. Exchange transfusions or dialysis may be required as a means of reversing hypotension and/or substituting for disordered renal function .

Chlorthalidone

Thiazides cross the placenta, and use of thiazides during pregnancy is associated with a risk of fetal or neonatal jaundice, thrombocytopenia, and possible other adverse reactions that have occurred in adults.

Data

Animal Data

Edarbyclor

The safety profiles of azilsartan medoxomil and chlorthalidone monotherapy have been individually established. To characterize the toxicological profile for Edarbyclor, a 13-week repeat-dose toxicity study was conducted in rats. The results of this study indicated that the combined administration of azilsartan medoxomil, M-II, and chlorthalidone resulted in increased exposures to chlorthalidone.

Pharmacologically-mediated toxicity, including suppression of body weight gain and decreased food consumption in male rats, and increases in blood urea nitrogen in both sexes, was enhanced by coadministration of azilsartan medoxomil, M-II, and chlorthalidone. With the exception of these findings, there were no toxicologically synergistic effects in this study.

In an embryo-fetal developmental study in rats, there was no teratogenicity or increase in fetal mortality in the litters of dams receiving azilsartan medoxomil, M-II and chlorthalidone concomitantly at maternally toxic doses.

Azilsartan medoxomil

Reproductive Toxicology:In peri- and postnatal rat development studies, adverse effects on pup viability, delayed incisor eruption and dilatation of the renal pelvis along with hydronephrosis were seen when azilsartan medoxomil was administered to pregnant and nursing rats at 1.2 times the MRHD on a mg/m^2basis. Reproductive toxicity studies indicated that azilsartan medoxomil was not teratogenic when administered at oral doses up to 1000 mg azilsartan medoxomil/kg/day to pregnant rats (122 times the MRHD on a mg/m^2basis) or up to 50 mg azilsartan medoxomil/kg/day to pregnant rabbits (12 times the MRHD on a mg/m^2basis). M-II also was not teratogenic in rats or rabbits at doses up to 3000 mg M-II/kg/day. Azilsartan crossed the placenta and was found in the fetuses of pregnant rats and was excreted into the milk of lactating rats.

Chlorthalidone

Reproductive toxicology: Reproduction studies have been performed in the rat and the rabbit at doses up to 420 times the human dose and have revealed no evidence of harm to the fetus. Thiazides cross the placental barrier and appear in cord blood.

8.2 Lactation

Risk Summary

There is limited information regarding the presence of azilsartan in human milk, the effects on the breastfed infant, or the effects on milk production. Azilsartan is present in rat milk. Thiazide-like diuretics like chlorthalidone are excreted in human milk. Because of the potential for adverse effects on the nursing infant, advise a nursing woman that breastfeeding is not recommended during treatment with Edarbyclor .

8.4 Pediatric Use

Safety and effectiveness of Edarbyclor in pediatric patients under 18 years of age have not been established.

8.5 Geriatric Use

Edarbyclor

No dose adjustment with Edarbyclor is necessary in elderly patients. Of the total patients in clinical studies with Edarbyclor, 24% were elderly (65 years of age or older); 5.7% were 75 years and older. No overall differences in safety or effectiveness were observed between elderly patients and younger patients, but greater sensitivity of some older individuals cannot be ruled out [see Clinical Pharmacology (12.3)].

8.6 Renal Impairment

Edarbyclor

Safety and effectiveness of Edarbyclor in patients with severe renal impairment (eGFR <30 mL/min/1.73 m^2) have not been established. No dose adjustment is required in patients with mild (eGFR 60-90 mL/min/1.73 m^2) or moderate (eGFR 30-60 mL/min/1.73 m^2) renal impairment.

Chlorthalidone

Chlorthalidone may precipitate azotemia.

8.7 Hepatic Impairment

Azilsartan medoxomil

No dose adjustment is necessary for subjects with mild or moderate hepatic impairment. Azilsartan medoxomil has not been studied in patients with severe hepatic impairment [see Clinical Pharmacology (12.3)].

Chlorthalidone

Minor alterations of fluid and electrolyte balance may precipitate hepatic coma in patients with impaired hepatic function or progressive liver disease.

10 OVERDOSAGE

Limited data are available related to overdosage in humans.

Azilsartan medoxomil

Limited data are available related to overdosage in humans. During controlled clinical trials in healthy subjects, once daily doses up to 320 mg of azilsartan medoxomil were administered for 7 days and were well tolerated. In the event of an overdose, supportive therapy should be instituted as dictated by the patient's clinical status. Azilsartan is not dialyzable.

Chlorthalidone

Symptoms of acute overdosage include nausea, weakness, dizziness, and disturbances of electrolyte balance. The oral LD50 of the drug in the mouse and the rat is more than 25,000 mg/kg body weight. The minimum lethal dose (MLD) in humans has not been established. There is no specific antidote, but gastric lavage is recommended, followed by supportive treatment. Where necessary, this may include intravenous dextrose-saline with potassium, administered with caution.

11 DESCRIPTION

Edarbyclor is a combination of azilsartan medoxomil (angiotensin II receptor blocker; as its potassium salt) and chlorthalidone (thiazide-like diuretic).

Azilsartan medoxomil, a prodrug, is hydrolyzed to azilsartan in the gastrointestinal tract during absorption. Azilsartan is an angiotensin II receptor blocker. Chlorthalidone is a monosulfamyl thiazide-like diuretic that differs chemically from thiazide diuretics by the lack of a benzothiadiazine structure.

The potassium salt of azilsartan medoxomil, azilsartan kamedoxomil, is chemically described as (5-Methyl-2-oxo-1,3-dioxol-4-yl)methyl 2-ethoxy-1-{[2'-(5-oxo-4,5-dihydro-1,2,4-oxadiazol-3-yl)biphenyl-4-yl]methyl}-1 H-benzimidazole-7-carboxylate monopotassium salt. Its empirical formula is C30H23KN4O8.

Chlorthalidone is chemically described as 2-chloro-5(1-hydroxy-3-oxo-1- isoindolinyl) benzenesulfonamide. Its empirical formula is C14H11ClN2O4S.

The structural formula for azilsartan medoxomil is

The structural formula for chlorthalidone is

Azilsartan kamedoxomil is a white to nearly white powder with a molecular weight of 606.62. It is practically insoluble in water and freely soluble in methanol.

Chlorthalidone is a white to yellowish white powder with a molecular weight of 338.76. Chlorthalidone is practically insoluble in water, in ether, and in chloroform; soluble in methanol; slightly soluble in ethanol.

Edarbyclor is available for oral use as tablets. The tablets have a characteristic odor. Each Edarbyclor tablet contains 42.68 mg of azilsartan kamedoxomil, which is equivalent to containing azilsartan medoxomil 40 mg plus 12.5 or 25 mg of chlorthalidone. Each tablet of Edarbyclor also contains the following inactive ingredients: mannitol, microcrystalline cellulose, fumaric acid, sodium hydroxide, hydroxypropyl cellulose, crospovidone, magnesium stearate, hypromellose 2910, talc, titanium dioxide, ferric oxide red, polyethylene glycol 8000, and printing ink gray F1.

12 CLINICAL PHARMACOLOGY

12.1 Mechanism of Action

The active ingredients of Edarbyclor target two separate mechanisms involved in blood pressure regulation.

Azilsartan medoxomil

Angiotensin II is formed from angiotensin I in a reaction catalyzed by angiotensin-converting enzymes (ACE, kinase II). Angiotensin II is the principle pressor agent of the renin-angiotensin system, with effects that include vasoconstriction, stimulation of synthesis and release of aldosterone, cardiac stimulation, and renal reabsorption of sodium. Azilsartan medoxomil is an orally administered prodrug that is rapidly converted by esterases during absorption to the active moiety, azilsartan. Azilsartan blocks the vasoconstrictor and aldosterone-secreting effects of angiotensin II by selectively blocking the binding of angiotensin II to the AT1receptor in many tissues, such as vascular smooth muscle and the adrenal gland. Its action is, therefore, independent of the pathway for angiotensin II synthesis.

An AT2receptor is also found in many tissues, but this receptor is not known to be associated with cardiovascular homeostasis. Azilsartan has more than a 10,000-fold greater affinity for the AT1receptor than for the AT2receptor.

Blockade of the renin-angiotensin system with ACE inhibitors, which inhibit the biosynthesis of angiotensin II from angiotensin I, is widely used in the treatment of hypertension. ACE inhibitors also inhibit the degradation of bradykinin, a reaction catalyzed by ACE. Because azilsartan does not inhibit ACE (kinase II), it should not affect bradykinin levels. Whether this difference has clinical relevance is not yet known. Azilsartan does not bind to or block other receptors or ion channels known to be important in cardiovascular regulation.

Blockade of the angiotensin II receptor inhibits the negative regulatory feedback of angiotensin II on renin secretion, but the resulting increased plasma renin activity and angiotensin II circulating levels do not overcome the effect of azilsartan on blood pressure.

Chlorthalidone

Chlorthalidone produces diuresis with increased excretion of sodium and chloride. The site of action appears to be the distal renal tubule (early convoluted part), inhibiting NaCl reabsorption (by antagonizing the Na+-Cl-cotransporter) and promoting Ca++ reabsorption (by an unknown mechanism). The enhanced delivery of Na+ and water to the cortical collecting tubule and/or the increased flow rate leads to increased secretion and elimination of K+ and H+. The diuretic effects of chlorthalildone lead to decreased extracellular fluid volume, plasma volume, cardiac output, total exchangeable sodium, glomerular filtration rate, and renal plasma flow. Although the mechanism of action of chlorthalidone and related drugs is not wholly clear, sodium and water depletion appear to provide a basis for its antihypertensive effect.

12.2 Pharmacodynamics

Edarbyclor

Edarbyclor tablets have been shown to be effective in lowering blood pressure. Both azilsartan medoxomil and chlorthalidone lower blood pressure by reducing peripheral resistance but through complementary mechanisms.

Azilsartan medoxomil

Azilsartan inhibits the pressor effects of an angiotensin II infusion in a dose-related manner. An azilsartan single dose equivalent to 32 mg azilsartan medoxomil inhibited the maximal pressor effect by approximately 90% at peak, and approximately 60% at 24 hours. Plasma angiotensin I and II concentrations and plasma renin activity increased while plasma aldosterone concentrations decreased after single and repeated administration of azilsartan medoxomil to healthy subjects; no clinically significant effects on serum potassium or sodium were observed.

Chlorthalidone

The diuretic effect of chlorthalidone occurs in approximately 2.6 hours and continues for up to 72 hours.

12.3 Pharmacokinetics

Edarbyclor

Following oral administration of Edarbyclor, peak plasma concentrations of azilsartan and chlorthalidone are reached at 3 and 1 hours, respectively. The rate (Cmaxand Tmax) and extent (AUC) of absorption of azilsartan are similar when it is administered alone or with chlorthalidone. The extent (AUC) of absorption of chlorthalidone is similar when it is administered alone or with azilsartan medoxomil; however, the Cmaxof chlorthalidone from Edarbyclor was 45-47% higher.

There is no clinically significant effect of food on the bioavailability of azilsartan or chlorthalidone following administration of Edarbyclor.

Azilsartan medoxomil

Absorption:Azilsartan medoxomil is an orally administered prodrug that is rapidly converted by esterases during absorption to the active moiety, azilsartan. Azilsartan medoxomil is not detected in plasma after oral administration. Dose proportionality in exposure was established for azilsartan in the azilsartan medoxomil dose range of 20 mg to 320 mg after single or multiple dosing.

The estimated absolute bioavailability of azilsartan following administration of azilsartan medoxomil is approximately 60%. After oral administration of azilsartan medoxomil, peak plasma concentrations (Cmax) of azilsartan are reached within 1.5 to 3 hours. Food does not affect the bioavailability of azilsartan.

Distribution

Azilsartan medoxomil:The volume of distribution of azilsartan is approximately 16L. Azilsartan is highly bound to human plasma proteins (>99%), mainly serum albumin. Protein binding is constant at azilsartan plasma concentrations well above the range achieved with recommended doses.

In rats, minimal azilsartan-associated radioactivity crossed the blood-brain barrier. Azilsartan passed across the placental barrier in pregnant rats and was distributed to the fetus.

Chlorthalidone:In whole blood, chlorthalidone is predominantly bound to erythrocyte carbonic anhydrase. In the plasma, approximately 75% of chlorthalidone is bound to plasma proteins, 58% of the drug being bound to albumin. Chlorthalidone crosses the placental barrier and passes into breast milk. When mothers were treated before and after birth with 50 mg chlorthalidone daily, chlorthalidone levels in fetal whole blood were around 15% of those found in maternal blood. Chlorthalidone concentrations in amniotic fluid and breast milk are approximately 4% of those found in maternal blood.

Metabolism and Elimination

Azilsartan medoxomil:Azilsartan medoxomil, when administered alone or in combination with chlorthalidone is eliminated from plasma with an elimination half-life of 11-13 hours. Azilsartan is metabolized to two primary metabolites. The major metabolite in plasma is formed by O-dealkylation, referred to as metabolite M-II, and the minor metabolite is formed by decarboxylation, referred to as metabolite M-I. Systemic exposures to the major and minor metabolites in humans were approximately 50% and less than 1% of azilsartan, respectively. M-I and M-II do not contribute to the pharmacologic activity of azilsartan medoxomil. The major enzyme responsible for azilsartan metabolism is CYP2C9.

Following an oral dose of^14C-labeled azilsartan medoxomil, approximately 55% of radioactivity was recovered in feces and approximately 42% in urine, with 15% of the dose excreted in urine as azilsartan. The elimination half-life of azilsartan is approximately 11 hours and renal clearance is approximately 2.3 mL/min. Steady-state levels of azilsartan are achieved within 5 days and no accumulation in plasma occurs with repeated once-daily dosing.

Chlorthalidone:Chlorthalidone when administered alone or in combination with azilsartan medoxomil is eliminated from plasma with an elimination half-life of 42-45 hours. The elimination half-life is unaltered following repeat dosing. The majority of an absorbed quantity of chlorthalidone is excreted by the kidneys with a mean renal clearance of 46-70 mL/min. By contrast, metabolism and excretion via the liver and bile play a minor role in the elimination of the substance. Approximately 60%-70% of chlorthalidone is excreted in the urine and feces within 120 hours, mainly in unchanged form.

Specific Populations

Azilsartan medoxomil:The effect of demographic and functional factors on the pharmacokinetics of azilsartan was studied in single and multiple dose studies. Pharmacokinetic measures indicating the magnitude of the effect on azilsartan are presented in Figure 2 as change relative to reference (test/reference).

Figure 2. Impact of intrinsic factors on the pharmacokinetics of azilsartan

Drug Interactions

Azilsartan medoxomil

No clinically significant drug interactions have been observed in studies of azilsartan medoxomil or azilsartan given with amlodipine, antacids, chlorthalidone, digoxin, fluconazole, glyburide, ketoconazole, metformin, pioglitazone, and warfarin. Therefore, azilsartan medoxomil may be used concomitantly with these medications .

13 NONCLINICAL TOXICOLOGY

13.1 Carcinogenesis, Mutagenesis, Impairment of Fertility

No carcinogenicity, mutagenicity, or fertility studies have been conducted with the combination of azilsartan medoxomil and chlorthalidone or with chlorthalidone alone. However, these studies have been conducted for azilsartan medoxomil, azilsartan and M-II.

Azilsartan medoxomil

Carcinogenesis:Azilsartan medoxomil was not carcinogenic when assessed in 26-week transgenic (Tg.rasH2) mouse and 2-year rat studies. The highest doses tested (450 mg azilsartan medoxomil/kg/day in the mouse and 600 mg azilsartan medoxomil/kg/day in the rat) produced exposures to azilsartan that are 12 (mice) and 27 (rats) times the average exposure to azilsartan in humans given the maximum recommended human dose (MRHD, 80 mg azilsartan medoxomil/day). M-II was not carcinogenic when assessed in 26-week Tg.rasH2 mouse and 2-year rat studies. The highest doses tested (approximately 8000 mg M-II/kg/day (males) and 11,000 mg M-II/kg/day (females) in the mouse and 1000 mg M-II/kg/day (males) and up to 3000 mg M-II/kg/day (females) in the rat) produced exposures that are, on average, about 30 (mice) and 7 (rats) times the average exposure to M-II in humans at the MRHD.

Mutagenesis:Chlorthalidone demonstrated no potential for mutagenic effects at non-cytotoxic concentrations and is considered not to pose a mutagenic risk to humans.

Azilsartan medoxomil, azilsartan, and M-II were positive for structural aberrations in the Chinese Hamster Lung Cytogenic Assay. In this assay, structural chromosomal aberrations were observed with the prodrug, azilsartan medoxomil, without metabolic activation. The active moiety, azilsartan, was also positive in this assay both with and without metabolic activation. The major human metabolite, M-II was also positive in this assay during a 24-hr assay without metabolic activation.

Azilsartan medoxomil, azilsartan, and M-II were devoid of genotoxic potential in the Ames reverse mutation assay with Salmonella typhimuriumand Escherichia coli, the in vitroChinese Hamster Ovary Cell forward mutation assay, the in vitromouse lymphoma (tk) gene mutation test, the ex vivounscheduled DNA synthesis test, and the in vivomouse and/or rat bone marrow micronucleus assay.

Impairment of Fertility:Chlorthalidone at a dosage of 100 mg/kg had no effect on fertility in rats .There was no effect of azilsartan medoxomil on the fertility of male or female rats at oral doses of up to 1000 mg azilsartan medoxomil/kg/day [6000 mg/m^2(approximately 122 times the MRHD of 80 mg azilsartan medoxomil/60 kg on a mg/m^2basis)]. Fertility of rats also was unaffected at doses of up to 3000 mg M-II/kg/day.

14 CLINICAL STUDIES

The antihypertensive effects of Edarbyclor have been demonstrated in a total of 5 randomized controlled studies, which included 4 double-blind, active-controlled studies and 1 open-label, long-term active-controlled study. The studies ranged from 8 weeks to 12 months in duration, at doses ranging from 20/12.5 mg to 80/25 mg once daily. A total of 5310 patients (3082 given Edarbyclor and 2228 given active comparator) with moderate or severe hypertension were studied. Overall, randomized patients had a mean age of 57 years, and included 52% males, 72% whites, 21% blacks, 15% with diabetes, 70% with mild or moderate renal impairment, and a mean BMI of 31.6 kg/m^2.

An 8-week, multicenter, randomized, double-blind, active-controlled, parallel group factorial trial in patients with moderate to severe hypertension compared the effect on blood pressure of Edarbyclor with the respective monotherapies. The trial randomized 1714 patients with baseline systolic blood pressure between 160 and 190 mm Hg (mean 165 mm Hg) and a baseline diastolic blood pressure <119 mm Hg (mean 95 mm Hg) to one of the 11 active treatment arms.

The 6 treatment combinations of azilsartan medoxomil 20, 40, or 80 mg and chlorthalidone 12.5 or 25 mg resulted in statistically significant reduction in systolic and diastolic blood pressure as determined by ambulatory blood pressure monitoring (ABPM) (Table 2) and clinic measurement (Table 3) at trough compared with the respective individual monotherapies. The clinic blood pressure reductions appear larger than those observed with ABPM, because the former include a placebo effect, which was not directly measured. Most of the antihypertensive effect of Edarbyclor occurs within 1-2 weeks of dosing. The blood pressure lowering effect was maintained throughout the 24-hour period (Figure 3).

Table 2. Mean Change from Baseline in Systolic/Diastolic Blood Pressure (mm Hg) as Measured by ABPM at Trough (22-24 Hours Post-Dose) at Week 8: Combination Therapy vs Monotherapy
Chlorthalidone, mg | Azilsartan Medoxomil, mg
Chlorthalidone, mg | 0 | 20 | 40 | 80
0 | N/A | -12 / -8 | -13 / -7 | -15 / -9
12.5 | -13 / -7 | -23 / -13 | -24 / -14 | -26 / -17
25 | -16 / -8 | -26 / -15 | -30 / -17 | -28 / -16

Table 3. Mean Change from Baseline in Clinic Systolic/Diastolic Blood Pressure (mm Hg) at Week 8: Combination Therapy vs Monotherapy
Chlorthalidone, mg | Azilsartan Medoxomil, mg
Chlorthalidone, mg | 0 | 20 | 40 | 80
0 | N/A | -20 / -7 | -23 / -9 | -24 / -10
12.5 | -21 / -7 | -34 / -14 | -37 / -16 | -37 / -17
25 | -27 / -9 | -37 / - 16 | -40 / -17 | -40 / -19

Figure 3. Mean Change from Baseline at Week 8 in Ambulatory Systolic Blood Pressure (mm Hg) by Treatment and Hour

Edarbyclor was effective in reducing blood pressure regardless of age, gender, or race.

Edarbyclor was effective in treating black patients (usually a low-renin population).

In a 12-week, double-blind forced-titration trial, Edarbyclor 40/25 mg was statistically superior (P<0.001) to olmesartan medoxomil – hydrochlorothiazide (OLM/HCTZ) 40/25 mg in reducing systolic blood pressure in patients with moderate to severe hypertension (Table 4). Similar results were observed in all subgroups, including age, gender, or race of patients.

Table 4. Mean Change in Systolic/Diastolic Blood Pressure (mm Hg) at Week 12
 | Edarbyclor 40/25 mg N=355 | OLM/HCTZ 40/25 mg N=364
Clinic (Mean Baseline 165/96 mm Hg) | -43 / -19 | -37 / -16
Trough by ABPM (22-24 hours) (Mean Baseline 153/92 mm Hg) | -33 / -20 | -26 / -16

Edarbyclor lowered blood pressure more effectively than OLM/HCTZ at each hour of the 24-hour interdosing period as measured by ABPM.

Cardiovascular Outcomes

There are no trials of Edarbyclor demonstrating reductions in cardiovascular risk in patients with hypertension; however, trials with chlorthalidone and at least one drug pharmacologically similar to azilsartan medoxomil have demonstrated such benefits.

16 HOW SUPPLIED/STORAGE AND HANDLING

Edarbyclor is supplied as fixed dose combination tablets that are round, biconvex, film-coated, and 9.7 mm in diameter.

Strength | Color | Imprinting | NDC Number
Strength | Color | Imprinting | Bottle of 30
40 / 12.5 mg | Pale red | A/C 40/12.5 | 60631-412-30
40 / 25 mg | Light red | A/C 40/25 | 75929-230-03

STORAGE AND HANDLING

Store at 25°C (77°F), excursions permitted to 15°-30°C (59°-86°F) [see USP Controlled Room Temperature].Keep container tightly closed. Protect from moisture and light. Do not repackage; dispense and store in original container.

17 PATIENT COUNSELING INFORMATION

See FDA-approved patient labeling (Patient Information).

Tell patients that if they miss a dose, they should take it later in the same day, but not to double the dose on the following day.

Pregnancy

Tell female patients of childbearing potential about the consequences of exposure to Edarbyclor during pregnancy. Discuss treatment options with women planning to become pregnant. Tell patients to report pregnancies to their physicians as soon as possible.

Symptomatic Hypotension

Advise patients to report light-headedness. Advise patients, if syncope occurs, to have someone call the doctor or seek medical attention, and to discontinue Edarbyclor.

Inform patients that dehydration from excessive perspiration, vomiting, or diarrhea may lead to an excessive fall in blood pressure. Inform patients to consult with their healthcare provider if these symptoms occur.

Patient Information EDARBYCLOR (eh-DAR-bih-clor) (azilsartan medoxomil and chlorthalidone) tablets

Read this Patient Information leaflet before you start taking Edarbyclor and each time you get a refill. There may be new information. This information does not take the place of talking to your doctor about your medical condition or your treatment.

What is the most important information I should know about Edarbyclor?

- Edarbyclor can cause harm or death to your unborn baby.
- Talk to your doctor about other ways to lower your blood pressure if you plan to become pregnant.
- If you become pregnant while taking Edarbyclor, tell your doctor right away. Your doctor may switch you to a different medicine to treat your high blood pressure.

What Is Edarbyclor?

Edarbyclor is a prescription medicine that contains azilsartan medoxomil, an angiotensin receptor blocker (ARB) and chlorthalidone, a water pill (diuretic).

Edarbyclor is used to treat high blood pressure (hypertension):

- when one medicine to lower your high blood pressure is not enough
- as the first medicine to lower your high blood pressure if your doctor decides you are likely to need more than one medicine.

It is not known if Edarbyclor is safe and effective in children under 18 years of age.

Who should not take Edarbyclor?

Do not take Edarbyclor if you:

- make less urine because of kidney problems

What should I tell my doctor before taking Edarbyclor?

Before you take Edarbyclor, tell your doctor if you:

- have been told that you have abnormal body salt (electrolytes) levels in your blood
- have liver or kidney problems
- have heart problems or stroke
- are vomiting or have diarrhea
- have gout
- are pregnant or plan to become pregnant. See " What is the most important information I should know about Edarbyclor?"
- are breastfeeding or plan to breastfeed. It is not known if Edarbyclor passes into your breast milk. You and your doctor should decide if you will take Edarbyclor or breastfeed. You should not do both. Talk with your doctor about the best way to feed your baby if you take Edarbyclor.

Tell your doctor about all the medicines you take, includingprescription and nonprescription medicines, vitamins, and herbal supplements.

Especially tell your doctor if you take:

- other medicines used to treat your high blood pressure or heart problem
- water pills (diuretics)
- lithium carbonate (Lithobid), lithium citrate
- digoxin (Lanoxin)

Ask your doctor if you are not sure if you are taking a medicine listed above.

Know the medicines you take. Keep a list of them and show it to your doctor or pharmacist when you get a new medicine.

How should I take Edarbyclor?

- Take Edarbyclor exactly as your doctor tells you to.
- Your doctor will tell you how much Edarbyclor to take and when to take it.
- Your doctor may prescribe other medicines for you to take along with Edarbyclor to treat your high blood pressure.
- Edarbyclor can be taken with or without food.
- If you miss a dose, take it later in the same day. Do not take more than 1 dose of Edarbyclor in a day.
- If you take too much Edarbyclor and have symptoms of low blood pressure (hypotension) and dizziness, call your doctor for advice. See " What are the possible side effects of Edarbyclor?"

What are the possible side effects of Edarbyclor?

Edarbyclor may cause serious side effects, including:

- See" What is the most important information I should know about Edarbyclor?"
- Low blood pressure (hypotension) and dizzinessis most likely to happen if you also:
  - take water pills (diuretics)
  - are on a low-salt diet
  - take other medicines that affect your blood pressure
  - sweat a lot
  - get sick with vomiting or diarrhea
  - do not drink enough fluids

If you feel faint or dizzy, lie down and call your doctor right away. If you pass out (faint) have someone call your doctor or get medical help. Stop taking Edarbyclor.

- Kidney problems.Kidney problems may become worse in people that already have kidney disease. Some people have changes in blood tests for kidney function and may need a lower dose of Edarbyclor or may need to stop treatment with Edarbyclor. During treatment with Edarbyclor, certain people who have severe heart failure, narrowing of the artery to the kidney, or who lose too much body fluid such as with nausea, vomiting, bleeding, or trauma, may develop sudden kidney failure and in rare instances, death.
- Fluid and body salt (electrolyte) problems.Tell your doctor if you get any of the following symptoms:
  - dry mouth
  - thirst
  - lack of energy (lethargic)
  - weakness
  - drowsiness
  - confusion
  - seizures
  - muscle pain or cramps
  - restlessness
  - muscle tiredness (fatigue)
  - passing very little urine or passing large amounts of urine
  - fast or abnormal heartbeat
  - nausea and vomiting
  - constipation
- Increased uric acid levels in the blood.People who have increased levels of uric acid in the blood may develop gout. If you already have gout, tell your doctor about worsening of your gout symptoms.

The most common side effects of Edarbyclor are:

- dizziness, and
- tiredness

These are not all the possible side effects with Edarbyclor. Tell your doctor if you have any side effect that bothers you or that does not go away.

Call your doctor for medical advice about side effects. You may report side effects to FDA at 1-800-FDA-1088.

How should I store Edarbyclor?

- Store Edarbyclor at room temperature between 68°F to 77°F (20°C to 25°C).
- Store Edarbyclor in the original container that you received from your pharmacist or doctor. Do not put Edarbyclor into a different container.
- Keep the container closed tightly, and keep Edarbyclor out of the light.

Keep Edarbyclor and all medicines out of the reach of children.

General information about Edarbyclor

Medicines are sometimes prescribed for purposes other than those listed in the Patient Information leaflet. Do not use Edarbyclor for a condition for which it was not prescribed. Do not give Edarbyclor to other people, even if they have the same symptoms you have. It may harm them.

This Patient Information leaflet summarizes the most important information about Edarbyclor. If you would like more information, talk with your doctor. You can ask your pharmacist or doctor for information about Edarbyclor that is written for health professionals.

For more information, go to www.edarbyclor.com or call 1-800-461-7449.

What is high blood pressure (hypertension)?

Blood pressure is the force in your blood vessels when your heart beats and when your heart rests. You have high blood pressure when the force is too great.

High blood pressure makes the heart work harder to pump blood through the body and causes damage to the blood vessels. Edarbyclor tablets can help your blood vessels relax so your blood pressure is lower. Medicines that lower your blood pressure may lower your chance of having a stroke or heart attack.

What are the ingredients in Edarbyclor?

Activeingredients :azilsartan medoxomil and chlorthalidone

Inactiveingredients :mannitol, microcrystalline cellulose, fumaric acid, sodium hydroxide, hydroxypropyl cellulose, crospovidone, magnesium stearate, hypromellose 2910, talc, titanium dioxide, ferric oxide red, polyethylene glycol 8000, and printing ink gray F1.

This Patient Information has been approved by the U.S. Food and Drug Administration.

Manufactured by:
Takeda
Ireland

Manufactured for:
azurity®
pharmaceuticals
Woburn, MA 01801

Patent: https://azurity.com/patents

Revised: April 2023

Edarbyclor is a trademark of Takeda Pharmaceutical Company Limited registered with the U.S. Patent and Trademark Office and used under license by Azurity Pharmaceuticals, Inc.

EC-PI-09

PRINCIPAL DISPLAY PANEL - 40 mg/12.5 mg Tablet Bottle Label

NDC 60631-412-30
30 Tablets

edarbyclor

Azilsartan Medoxomil and
Chlorthalidone Tablets

40 mg*/12.5 mg

Rx Only

*Each tablet contains:
42.68 mg azilsartan kamedoxomil
(equivalent to 40 mg
azilsartan medoxomil) and
12.5 mg chlorthalidone.

Dispense
and store
in original
container.

PRINCIPAL DISPLAY PANEL - 40 mg/25 mg Tablet Bottle Label

NDC 75929-230-03
30 Tablets

edarbyclor

Azilsartan Medoxomil and
Chlorthalidone Tablets

40 mg* /25 mg

Rx Only

*Each tablet contains:
42.68 mg azilsartan kamedoxomil
(equivalent to 40 mg
azilsartan medoxomil) and
25 mg chlorthalidone.

Dispense
and store
in original
container.